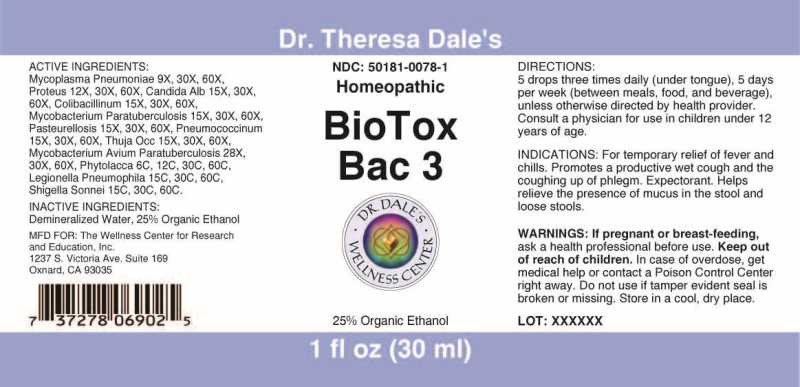 DRUG LABEL: BioTox Bac
NDC: 50181-0078 | Form: LIQUID
Manufacturer: The Wellness Center for Research and Education, Inc.
Category: homeopathic | Type: HUMAN OTC DRUG LABEL
Date: 20250606

ACTIVE INGREDIENTS: MYCOPLASMA PNEUMONIAE 9 [hp_X]/1 mL; PROTEUS INCONSTANS 12 [hp_X]/1 mL; CANDIDA ALBICANS 15 [hp_X]/1 mL; ESCHERICHIA COLI 15 [hp_X]/1 mL; MYCOBACTERIUM AVIUM SUBSP. PARATUBERCULOSIS 15 [hp_X]/1 mL; PASTEURELLA MULTOCIDA 15 [hp_X]/1 mL; STREPTOCOCCUS PNEUMONIAE 15 [hp_X]/1 mL; THUJA OCCIDENTALIS LEAFY TWIG 15 [hp_X]/1 mL; PHYTOLACCA AMERICANA ROOT 6 [hp_C]/1 mL; LEGIONELLA PNEUMOPHILA 15 [hp_C]/1 mL; SHIGELLA SONNEI 15 [hp_C]/1 mL
INACTIVE INGREDIENTS: WATER; ALCOHOL

DRUG FACTS:

ACTIVE INGREDIENTS:

Mycoplasma Pneumoniae 9X, 30X, 60X, Proteus (Vulgaris) 12X, 30X, 60X, Candida Albicans 15X, 30X, 60X, Colibacillinum Cum Natrum Muriaticum 15X, 30X, 60X, Mycobacterium Paratuberculosis 15X, 30X, 60X, Pasteurellosis (Pasteurella Multocida) 15X, 30X, 60X, Pneumococcinum 15X, 30X, 60X, Thuja Occidentalis 15X, 30X, 60X, Mycobacterium Avium Paratuberculosis 28X, 30X, 60X, Phytolacca Decandra 6C, 12C, 30C, 60C, Legionella Pneumophila 15C, 30C, 60C, Shigella Sonnei 15C, 30C, 60C.

INDICATIONS:

For temporary relief of fever and chills. Promotes a productive wet cough and the coughing up of phlegm. expectorant. Helps relieve the presence of mucus in the stool and loose stools.

WARNINGS:

If pregnant or breast-feeding, ask a health professional before use.

Keep out of reach of children. In case of overdose, get medical help or contact a Poison Control Center right away.

Do not use if tamper evident seal is broken or missing.

Store in a cool, dry place.

Keep out of reach of children. In case of overdose, get medical help or contact a Poison Control Center right away.

DIRECTIONS:

5 drops three times daily (under tongus), 5 days per week (between meals, food and beverage), unless otherwise directed by health provider.

Consult a physician for use in children under 12 years of age.

INDICATIONS:

For temporary relief of fever and chills. Promotes a productive wet cough and the coughing up of phlegm. expectorant. Helps relieve the presence of mucus in the stool and loose stools.

INACTIVE INGREDIENTS:

Demineralized Water, 25% Organic Ethanol

QUESTONS:

MFD FOR: The Wellness Center for

Research and Education, Inc.

1237 S. Victoria Ave. Suite 169

Oxnard, CA 93035

PACKAGE LABEL DISPLAY:

Dr. Theresa Dale's

NDC 50181-0078-1

Homeopathic

BioTox Bac 3

1 fl oz (30 ml)